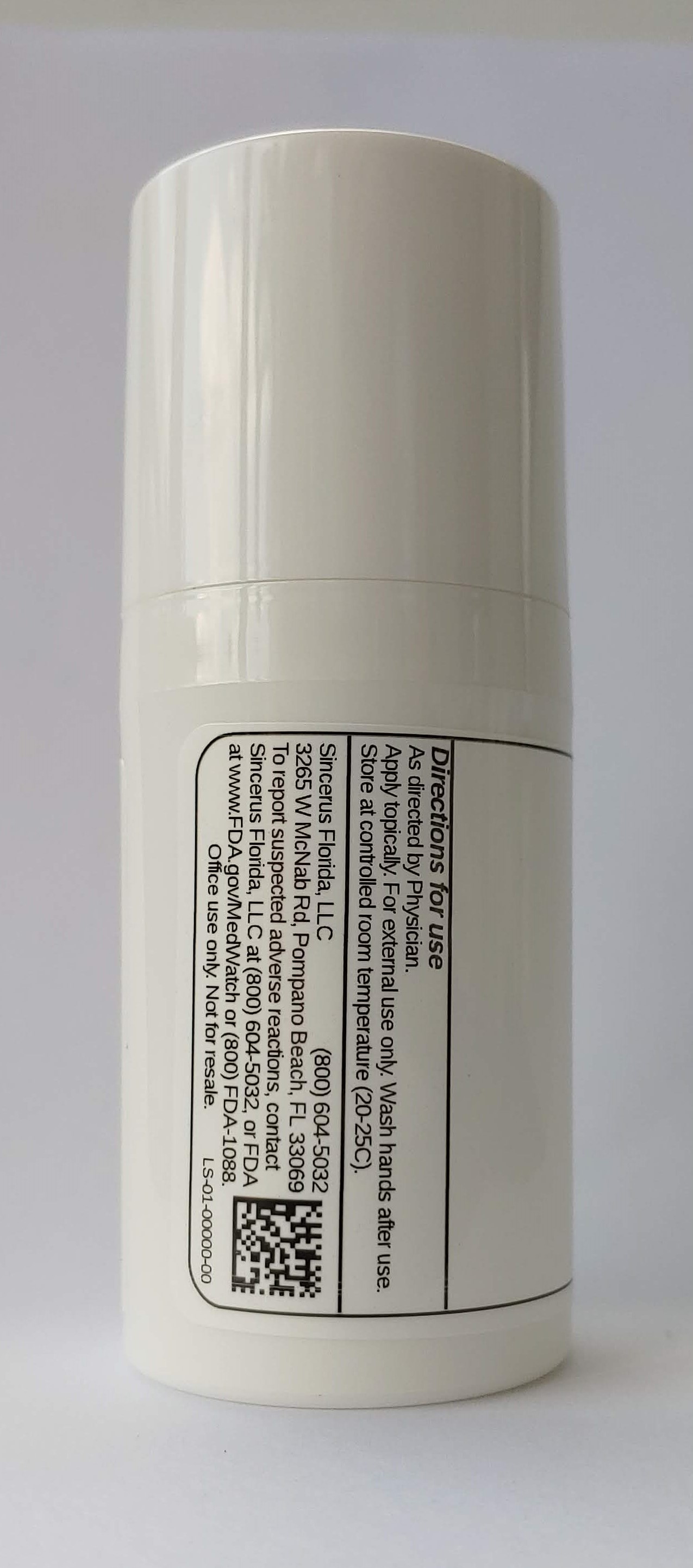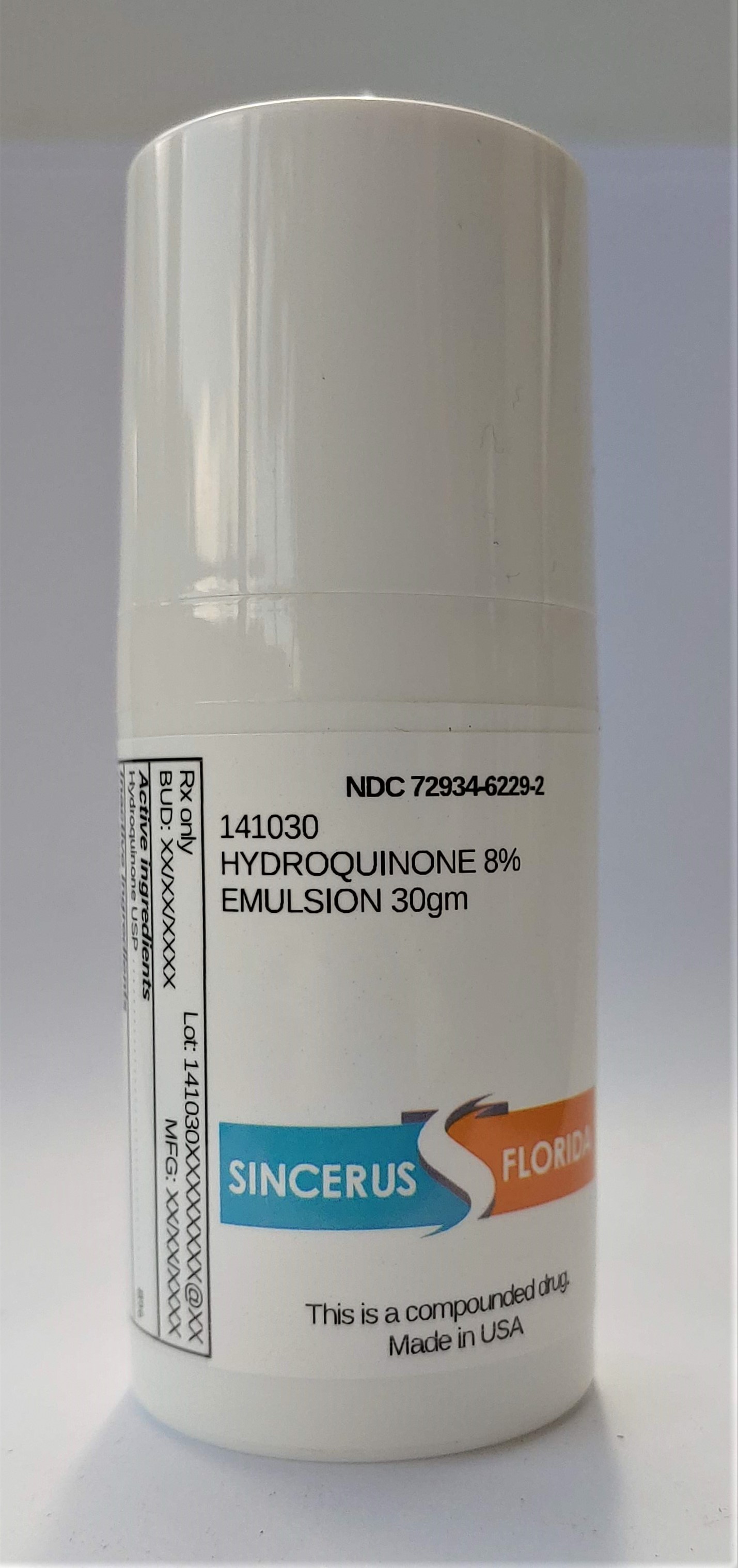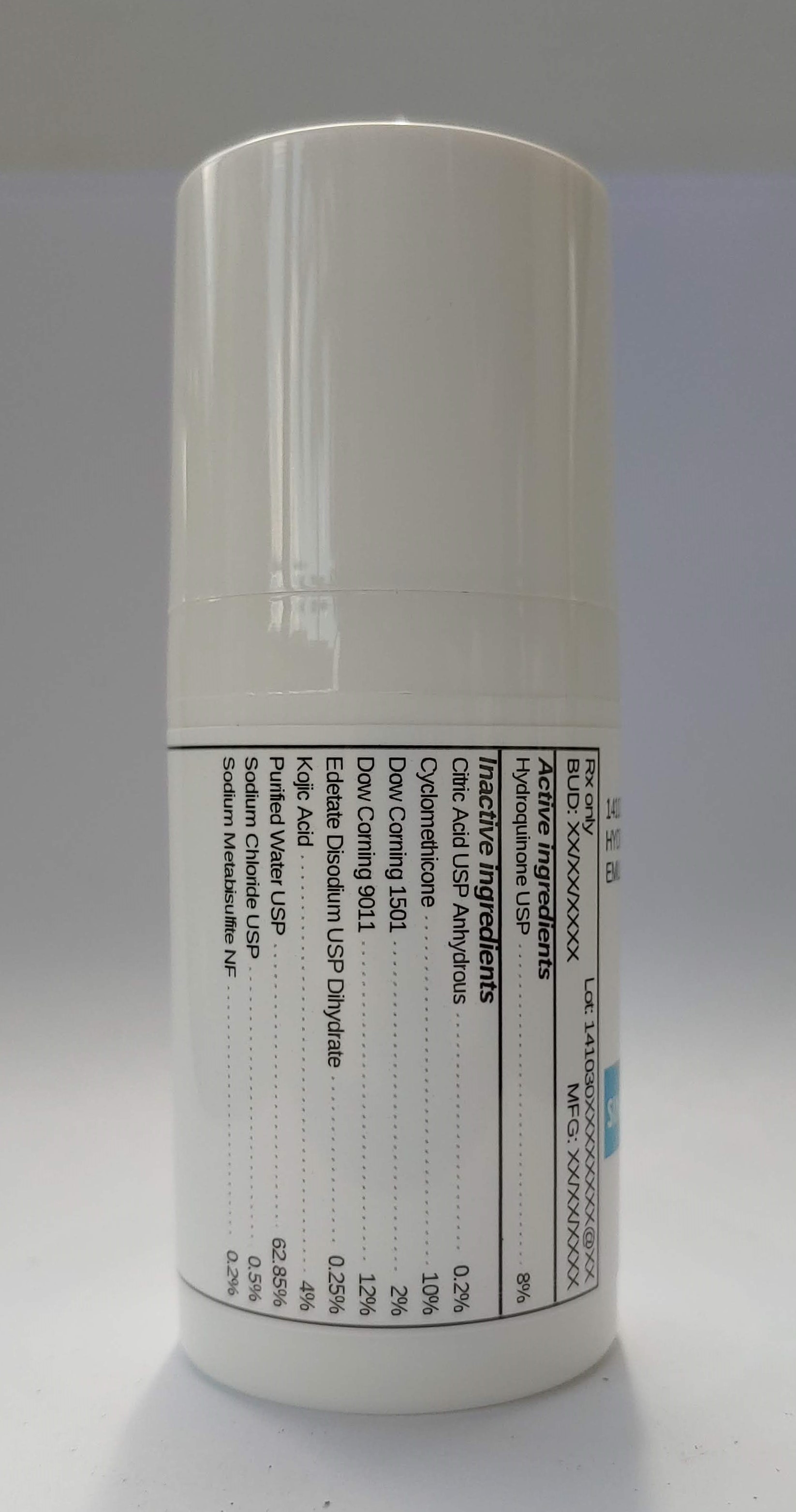 DRUG LABEL: 141030 HYDROQUINONE 8%
NDC: 72934-6229 | Form: EMULSION
Manufacturer: Sincerus Florida, LLC
Category: prescription | Type: HUMAN PRESCRIPTION DRUG LABEL
Date: 20200702

ACTIVE INGREDIENTS: HYDROQUINONE 8 g/100 g

141030 HYDROQUINONE 8%